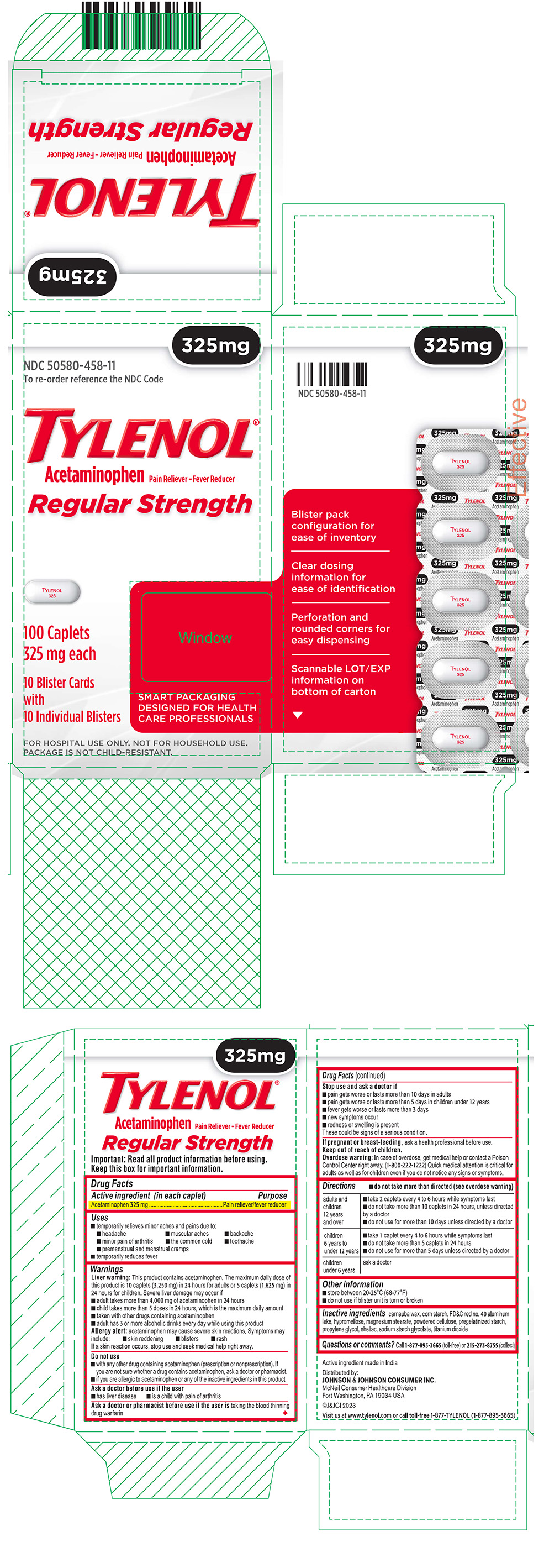 DRUG LABEL: TYLENOL
NDC: 50580-458 | Form: TABLET, FILM COATED
Manufacturer: Kenvue Brands LLC
Category: otc | Type: HUMAN OTC DRUG LABEL
Date: 20260126

ACTIVE INGREDIENTS: ACETAMINOPHEN 325 mg/1 1
INACTIVE INGREDIENTS: CARNAUBA WAX; STARCH, CORN; FD&C RED NO. 40; ALUMINUM OXIDE; HYPROMELLOSE, UNSPECIFIED; MAGNESIUM STEARATE; POWDERED CELLULOSE; PROPYLENE GLYCOL; SHELLAC; TITANIUM DIOXIDE; SODIUM STARCH GLYCOLATE TYPE A

TYLENOL Regular Strength

Drug Facts

Active ingredient (in each caplet)

Acetaminophen 325 mg

Purpose

Pain reliever/fever reducer

Uses

- temporarily relieves minor aches and pains due to:
  - headache
  - muscular aches
  - backache
  - minor pain of arthritis
  - the common cold
  - toothache
  - premenstrual and menstrual cramps
- temporarily reduces fever

Warnings

Liver warning

This product contains acetaminophen. The maximum daily dose of this product is 10 caplets (3,250 mg) in 24 hours for adults or 5 caplets (1,625 mg) in 24 hours for children. Severe liver damage may occur if

- adult takes more than 4,000 mg of acetaminophen in 24 hours
- child takes more than 5 doses in 24 hours, which is the maximum daily amount
- taken with other drugs containing acetaminophen
- adult has 3 or more alcoholic drinks every day while using this product

Allergy alert: acetaminophen may cause severe skin reactions. Symptoms may include:

- skin reddening
- blisters
- rash

If a skin reaction occurs, stop use and seek medical help right away.

Do not use

- with any other drug containing acetaminophen (prescription or nonprescription). If you are not sure whether a drug contains acetaminophen, ask a doctor or pharmacist.
- if you are allergic to acetaminophen or any of the inactive ingredients in this product

Ask a doctor before use if the user

- has liver disease
- is a child with pain of arthritis

Ask a doctor or pharmacist before use if the user is taking the blood thinning drug warfarin

Stop use and ask a doctor if

- pain gets worse or lasts more than 10 days in adults
- pain gets worse or lasts more than 5 days in children under 12 years
- fever gets worse or lasts more than 3 days
- new symptoms occur
- redness or swelling is present

These could be signs of a serious condition.

PREGNANCY OR BREAST FEEDING

If pregnant or breast-feeding, ask a health professional before use.

Keep out of reach of children.

Overdose warning

In case of overdose, get medical help or contact a Poison Control Center right away. (1-800-222-1222) Quick medical attention is critical for adults as well as for children even if you do not notice any signs or symptoms.

Directions

- do not take more than directed (see overdose warning)

adults and children 12 years and over | - take 2 caplets every 4 to 6 hours while symptoms last - do not take more than 10 caplets in 24 hours, unless directed by a doctor - do not use for more than 10 days unless directed by a doctor
children 6 years to under 12 years | - take 1 caplet every 4 to 6 hours while symptoms last - do not take more than 5 caplets in 24 hours - do not use for more than 5 days unless directed by a doctor
children under 6 years | ask a doctor

Other information

- store between 20-25°C (68-77°F)
- do not use if blister unit is torn or broken

Inactive ingredients

carnauba wax, corn starch, FD&C red no. 40 aluminum lake, hypromellose, magnesium stearate, powdered cellulose, pregelatinized starch, propylene glycol, shellac, sodium starch glycolate, titanium dioxide

Questions or comments?

Call 1-877-895-3665 (toll-free) or 215-273-8755 (collect)

PRINCIPAL DISPLAY PANEL

325mg

NDC 50580-458-11
To re-order reference the NDC Code

TYLENOL®

Acetaminophen Pain Reliever - Fever Reducer

Regular Strength

100 Caplets
325 mg each

10 Blister Cards
with
10 Individual Blisters

SMART PACKAGING
DESIGNED FOR HEALTH
CARE PROFESSIONALS

FOR HOSPITAL USE ONLY. NOT FOR HOUSEHOLD USE.

PACKAGE IS NOT CHILD-RESISTANT.